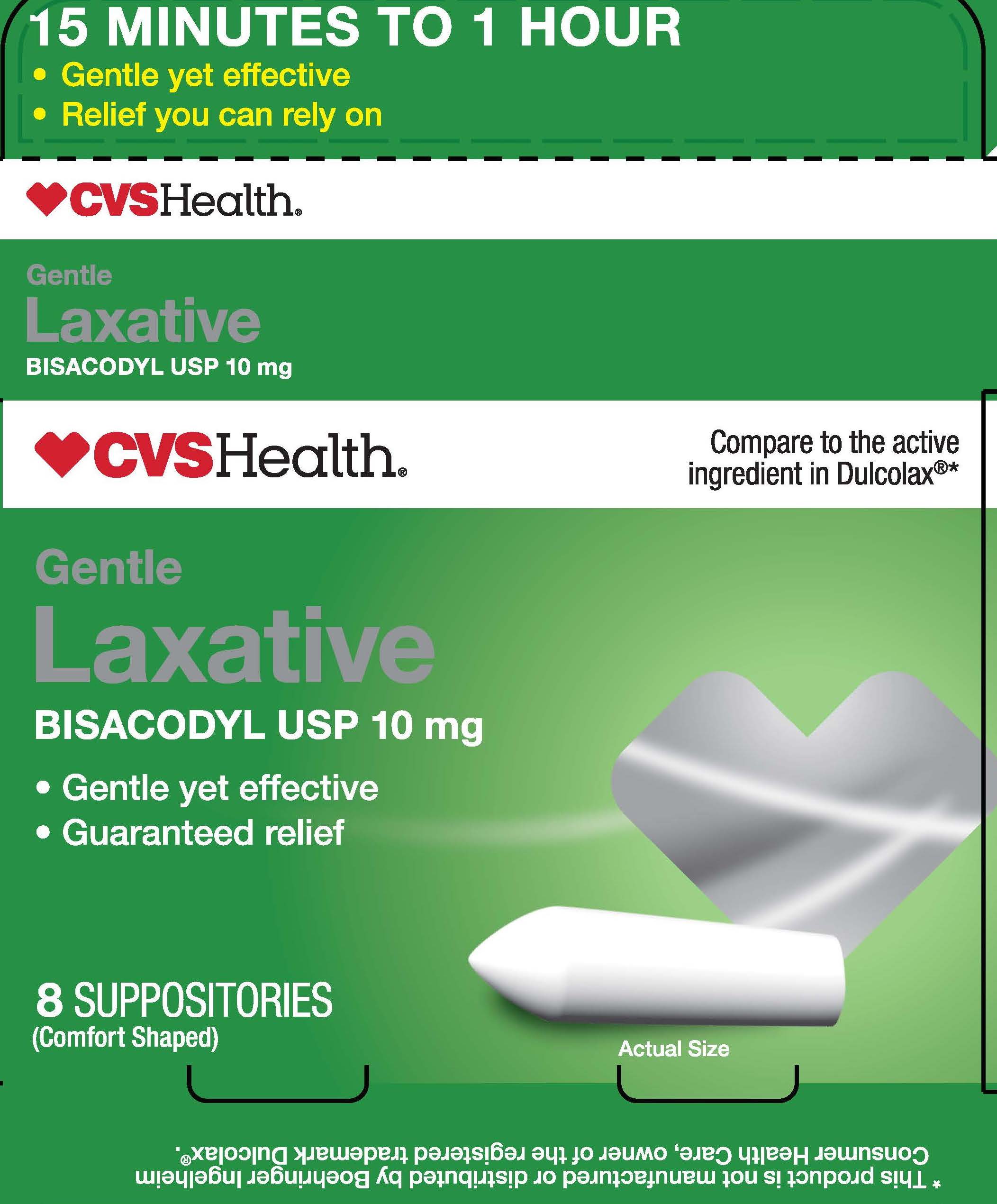 DRUG LABEL: Bisacodyl							
NDC: 69842-816 | Form: SUPPOSITORY
Manufacturer: CVS Pharmacy
Category: otc | Type: HUMAN OTC DRUG LABEL
Date: 20251024

ACTIVE INGREDIENTS: BISACODYL 10 mg/1 1
INACTIVE INGREDIENTS: HYDROGENATED PALM KERNEL OIL

CVS Bisacodyl Suppositories

Active ingredient (in each suppository)

Bisacodyl USP 10mg

Purpose

Stimulant Laxative

Use

- for temporary relief of occasional constipation
- this product generally produces bowel movement in 15 minutes to 1 hour

Warnings

For rectal use only

Do not use unless directed by a doctor

- if abdominal pain, nausea or vomiting are present
- for longer than 1 week

Ask a doctor before use if you have

noticed a sudden change in bowel habits that last over a period 2 weeks

When using this product

it may cause stomach discomfort, faintness, rectal burning and mild cramps

Stop use and ask a doctor if

you have rectal bleeding or fail to have a bowel movement after using this product. These may indicate a serious condition.

If pregnant or breast feeding,

ask a health professional before use.

Keep out of reach of children.

If swallowed, get medical help or contact a Poison Control Center right away.

Directions

- detach one suppository from the strip
- remove wrapper berore inserting into rectum

adults and children 12 years of age and over - 1 suppository once daily

children 6 to under 12 years of age - 1/2 suppository once daily

children under 6 years of age - do not use

Other information

- Store at room temeratur. Do not exceed 30ºC (86ºF)
- Lot No. & Exp. Date: see wrapper or box

Inactive ingredients

hydrogenated vegetable oil

CVS Bisacodyl Suppositories

CVSBisacodyl8ct.jpg

The product package shown above represents a sample of that currently in use. Additional packaging may also be available.

Bisacodyl Suppositories 8ct

Distributed by

CVS Pharmacy

One CVS Drive

Woonsocket, RI 02895